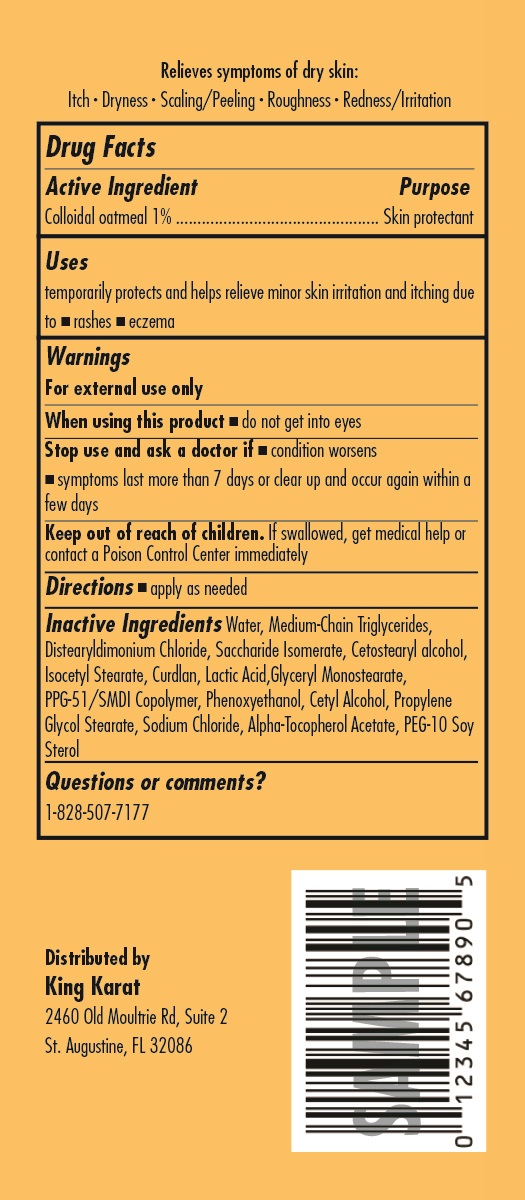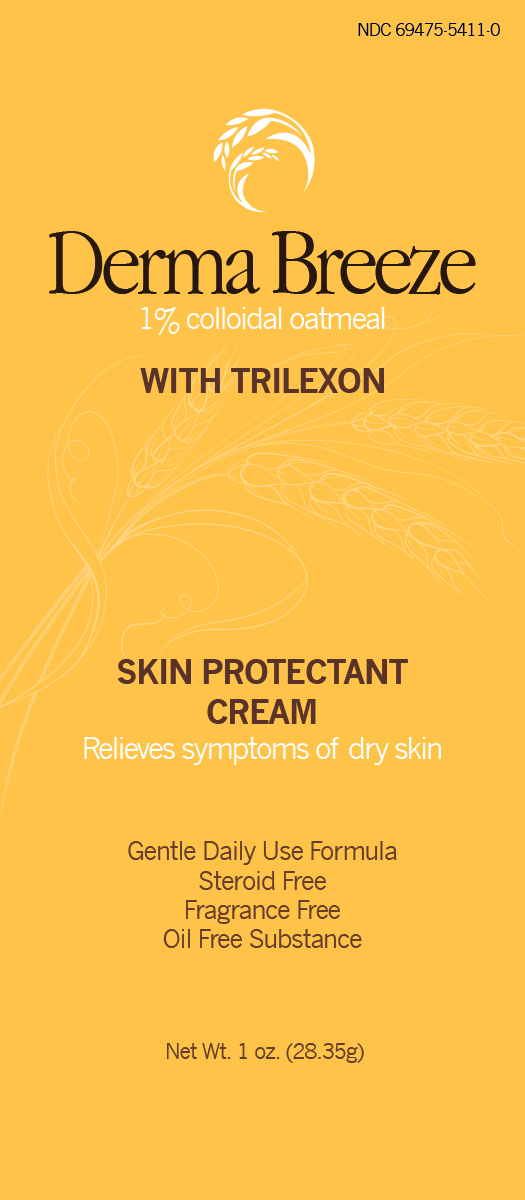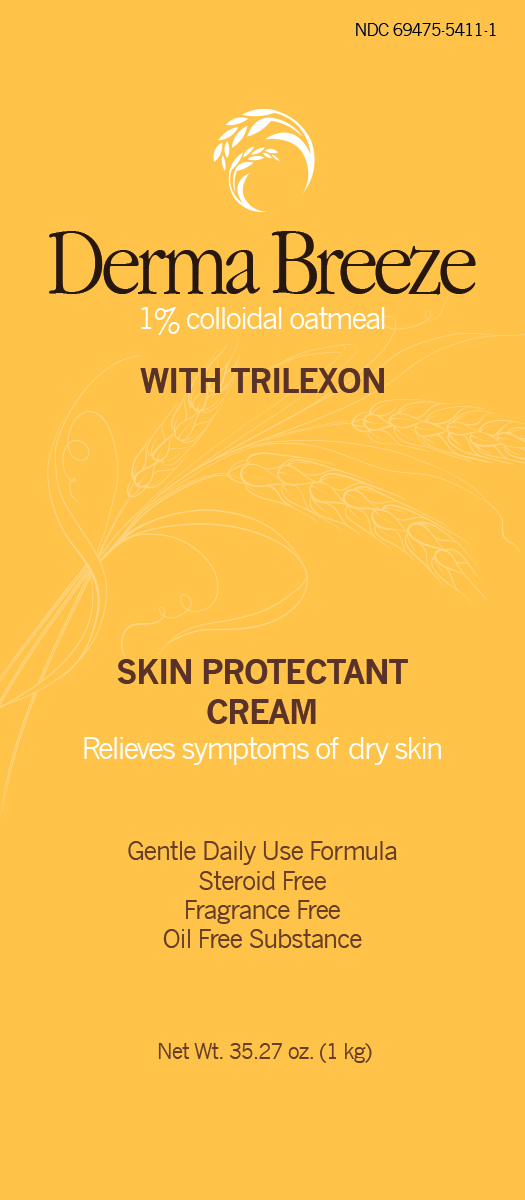 DRUG LABEL: Derma Breeze Skin Protectant Cream
NDC: 69475-5411 | Form: CREAM
Manufacturer: Greyson International, Inc.
Category: otc | Type: HUMAN OTC DRUG LABEL
Date: 20151120

ACTIVE INGREDIENTS: OATMEAL 10 mg/1 g
INACTIVE INGREDIENTS: DISTEARYLDIMONIUM CHLORIDE; CETYL ALCOHOL; CURDLAN; MEDIUM-CHAIN TRIGLYCERIDES; CETOSTEARYL ALCOHOL; ISOCETYL STEARATE; SACCHARIDE ISOMERATE; LACTIC ACID; GLYCERYL MONOSTEARATE; PPG-51/SMDI COPOLYMER; WATER; PHENOXYETHANOL; PROPYLENE GLYCOL STEARATE; SODIUM CHLORIDE; ALPHA-TOCOPHEROL ACETATE; PEG-10 SOY STEROL

Derma Breeze 1% colloidal oatmeal with Trilexon

Drug Facts

Active ingredient

Colloidal oatmeal 1%

Purpose

Skin protectant

Uses

temporarily protects and helps relieve minor skin irritation and itching due to:

- rashes
- eczema

Warnings

For external use only

When using this product

- do not get into eyes

Stop use and ask a doctor if

- condition worsens
- symptoms last more than 7 days or clear up and occur again within a few days.

Keep out of reach of children. If swallowed, get medical help or contact a Poison Control Center immediately

Directions

- apply as needed

Inactive ingredients

Water, Medium-Chain Triglycerides, Distearyldimonium Chloride, Saccharide Isomerate, Cetostearyl alcohol, Isocetyl Stearate, Curdlan, Lactic Acid,Glyceryl Monostearate, PPG-51/SMDI Copolymer, Phenoxyethanol, Cetyl Alcohol, Propylene Glycol Stearate, Sodium Chloride, Alpha-Tocopherol Acetate, PEG-10 Soy Sterol

Questions or comments?

1-828-507-7177

PRINCIPAL DISPLAY PANEL

Derma Breeze

1% colloidal oatmeal

WITH TRILEXON

SKIN PROTECTANT

CREAM

Relieves symptoms of dry skin

Gentle Daily Use Formula

Steroid Free

Fragrance Free

Oil Free Substance